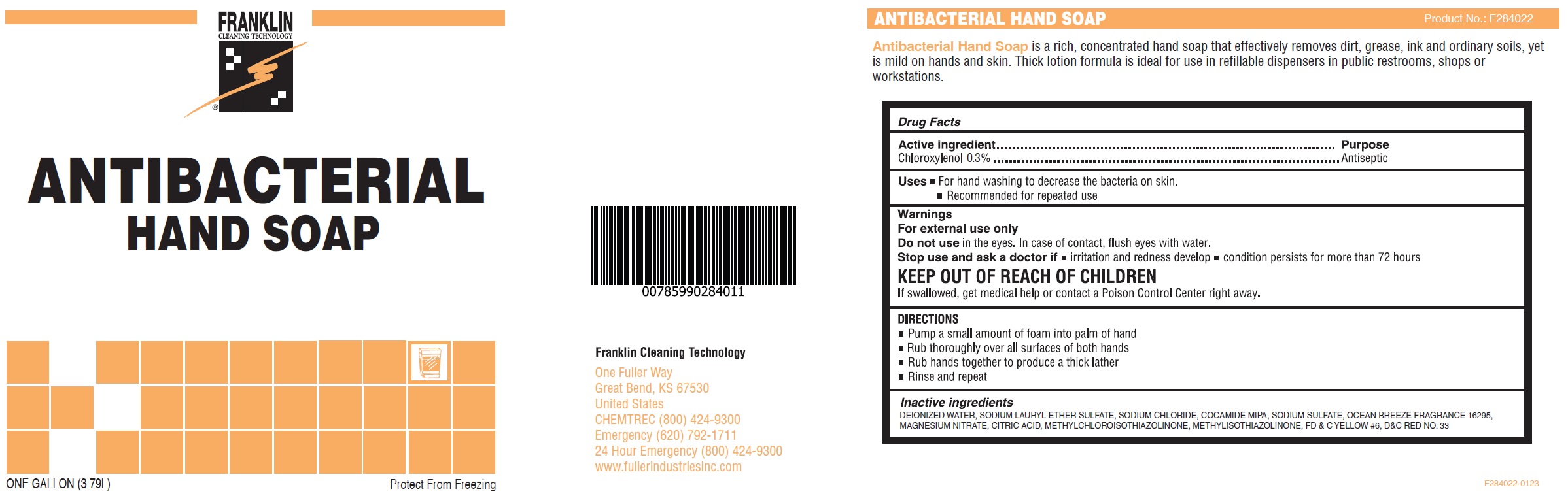 DRUG LABEL: Franklin cleaning technology antibacterial hand
NDC: 60933-056 | Form: LIQUID
Manufacturer: Fuller Industries, Inc
Category: otc | Type: HUMAN OTC DRUG LABEL
Date: 20231028

ACTIVE INGREDIENTS: CHLOROXYLENOL 3 mg/1 mL
INACTIVE INGREDIENTS: WATER; SODIUM LAURETH-3 SULFATE; SODIUM CHLORIDE; COCO MONOISOPROPANOLAMIDE; SODIUM SULFATE; MAGNESIUM NITRATE; CITRIC ACID MONOHYDRATE; METHYLCHLOROISOTHIAZOLINONE; METHYLISOTHIAZOLINONE; FD&C YELLOW NO. 6; D&C RED NO. 33

Franklin cleaning technology antibacterial hand soap

Active ingredient

Chloroxylenol 0.3%

Purpose

Antiseptic

Uses

- For hand washing to decrease the bacteria on skin.
- Recommended for repeated use

Warnings

For external use only

Do not use

in the eyes. In case of contact, flush eyes with water.

Stop use and ask a doctor if

- irritation and redness develop
- condition persists for more than 72 hours

KEEP OUT OF REACH OF CHILDREN

If swallowed, get medical help or contact a Poison Control Center right away.

DIRECTIONS

- Pump a small amount of foam into palm of hand
- Rub thoroughly over all surfaces of both hands
- Rub hands together to produce a thick lather
- Rinse and repeat

Inactive ingredients

DEIONIZED WATER, SODIUM LAURYL ETHER SULFATE, SODIUM CHLORIDE, COCAMIDE MIPA, SODIUM SULFATE, OCEAN BREEZE FRAGRANCE 16295, MAGNESIUM NITRATE, CITRIC ACID, METHYLCHLOROISOTHIAZOLINONE, METHYLISOTHIAZOLINONE, FD & C YELLOW #6, D&C RED NO. 33